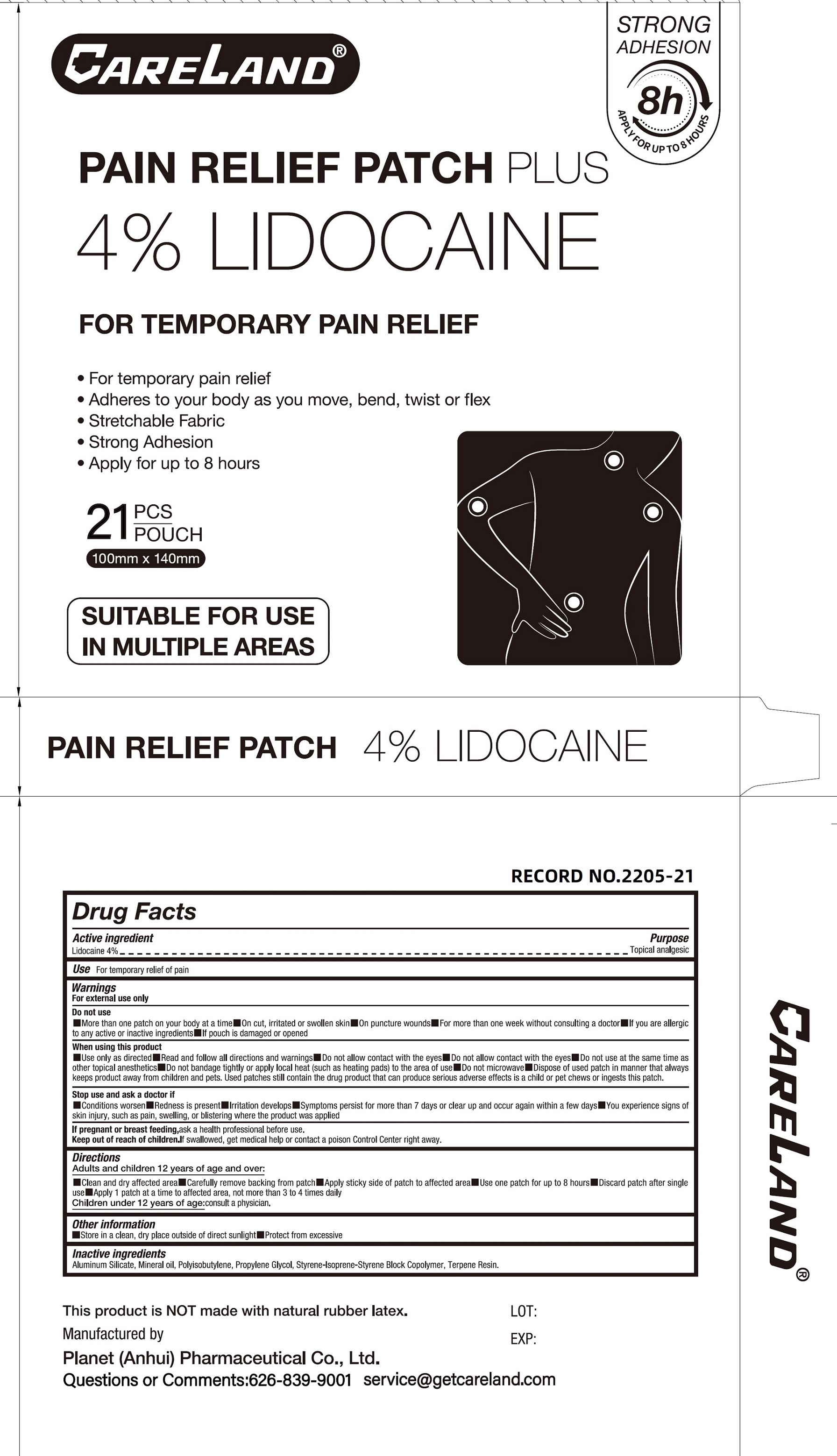 DRUG LABEL: Careland Pain Relief Patch Plus
NDC: 75568-038 | Form: PATCH
Manufacturer: Planet (Anhui) Pharmaceutical Co., Ltd.
Category: otc | Type: HUMAN OTC DRUG LABEL
Date: 20250926

ACTIVE INGREDIENTS: LIDOCAINE 40 mg/1 g
INACTIVE INGREDIENTS: ALUMINUM SILICATE; MINERAL OIL; PROPYLENE GLYCOL; STYRENE/ISOPRENE/STYRENE BLOCK COPOLYMER; TERPENE RESIN

Careland Pain Relief Patch Plus

Active ingredient

Lidocaine 4%

Purpose

Topical analgesic

Use

For temporary relief of pain

Warnings

For external use only

Do not use

- More than one patch on your body at a time
- On cut, irritated or swollen skin
- On puncture wounds
- For more than one week without consulting a doctor
- If you are allergic to any active or inactive ingredients
- If pouch is damaged or opened

When using this product

- Use only as directed
- Read and follow all directions and warnings
- Do not allow contact with the eyes
- Do not use at the same time as other topical anesthetics
- Do not bandage tightly or apply local heat (such as heating pads) to the area of use
- Do not microwave
- Dispose of used patch in manner that always keeps product away from children and pets. Used patches still contain the drug product that can produce serious adverse effects if a child or pet chews or ingests this patch.

Stop use and ask a doctor if

- Condition worsen
- Redness is present
- Irritation develops
- Symptoms persist for more than 7 days or clear up and occur again within a few days
- You experience signs of skin injury, such as pain, swelling, or blistering where the product was applied

If pregnant or breast feeding,

ask a health professional before use.

Keep out of reach of children.

If swallowed, get medical help or contact a poison Control Center right away.

Directions

Adults and children 12 years of age and over:

- Clean and dry affected area
- Carefully remove backing from patch
- Apply sticky side of patch to affected area
- Use one patch for up to 8 hours
- Discard patch after single use
- Apply 1 patch at a time to affected area, not more than 3 to 4 times daily
- Children under 12 years of age:consult a physician.

Other information

- Store in a clean, dry place outside of direct sunlight
- Protect from excessive

Inactive ingredients

Aluminum Silicate, Mineral oil, Polyisobutylene, Propylene Glycol, Styrene-Isoprene-Styrene Block Copolymer, Terpene Resin.